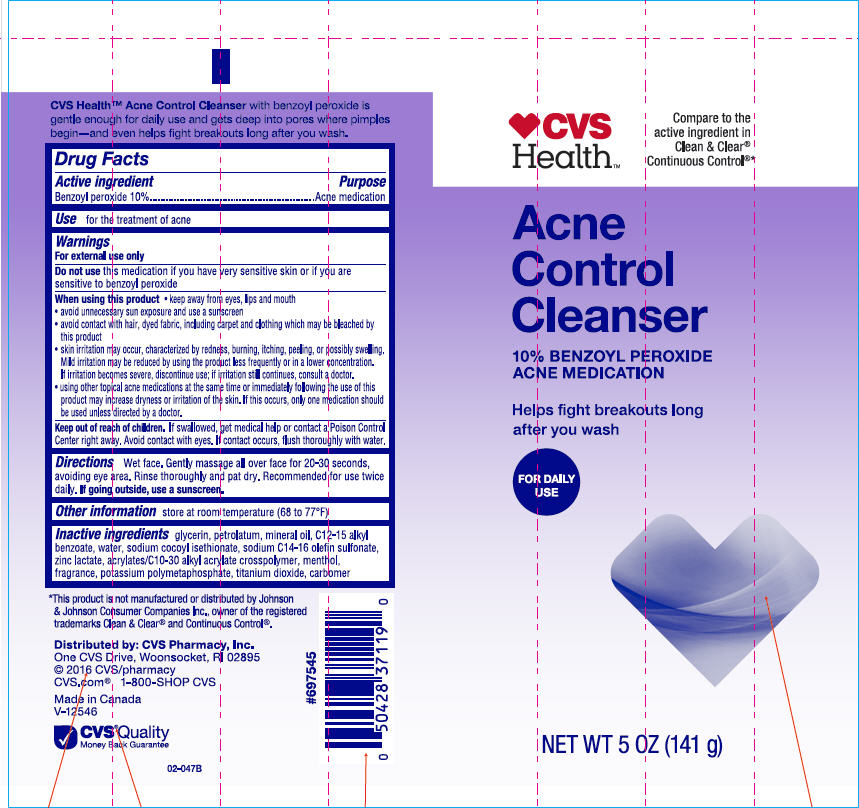 DRUG LABEL: CVS Health Acne Control Cleanser
NDC: 69842-571 | Form: LOTION
Manufacturer: CVS Health
Category: otc | Type: HUMAN OTC DRUG LABEL
Date: 20241112

ACTIVE INGREDIENTS: Benzoyl Peroxide 100 mg/1 g
INACTIVE INGREDIENTS: Glycerin; Petrolatum; Mineral Oil; Alkyl (C12-15) Benzoate; Water; Sodium Cocoyl Isethionate; Sodium C14-16 Olefin Sulfonate; Zinc Lactate; Carbomer Interpolymer Type A (Allyl Sucrose Crosslinked); Menthol, Unspecified Form; Potassium Metaphosphate; Titanium Dioxide; Carbomer Homopolymer Type C (Allyl Pentaerythritol Crosslinked)

CVS Health Acne Control Cleanser
Acne Medication

Drug Facts

Active ingredient

Benzoyl peroxide 10%

Purpose

Acne medication

Use

for the treatment of acne

Warnings

For external use only

Do not use this medication if you have very sensitive skin or if you are sensitive to benzoyl peroxide.

When using this product keep away from eyes, lips and mouth

- avoid unnecessary sun exposure and use a sunscreen
- avoid contact with hair or dyed fabric, including carpet and clothing which may be bleached by this product
- skin irritation may occur, characterized by redness, burning, itching, peeling, or possibly swelling. Mild irritation may be reduced by using the product less frequently or in a lower concentration. If irritation becomes severe, discontinue use; if irritation still continues, consult a doctor.
- using other topical acne medication at the same time or immediately following the use of this product may increase dryness or irritation of the skin. If this occurs, only one medication should be used unless directed by a doctor.

Keep out of reach of children. If swallowed, get medical help or contact a Poison Control Center right away. Avoid contact with the eyes. If contact occurs, flush thoroughly with water.

Directions

Wet face. Gently massage all over face for 20-30 seconds, avoiding eye area. Rinse thoroughly and pat dry. Recommended for use twice daily. If going outside, use a sunscreen.

Other information

store at room temperature (68 to 77°F).

Inactive ingredients

Glycerin, Petrolatum, Mineral Oil, C12-15 Alkyl Benzoate, Water, Sodium Cocoyl Isethionate, Sodium C14-16 Olefin Sulfonate, Zinc Lactate, Acrylates/C10-30 Alkyl Acrylate Crosspolymer, Menthol, Fragrance, Potassium Polymetaphosphate, Titanium Dioxide, Carbomer.

Distributed by: CVS Pharmacy, Inc.
One CVS Drive, Woonsocket, RI 02895

PRINCIPAL DISPLAY PANEL - 141 g Tube Label

♥CVS
Health™

Compare to the
active ingredient in
Clean & Clear®
Continuous Control®*

Acne
Control
Cleanser

10% BENZOYL PEROXIDE
ACNE MEDICATION

Helps fight breakouts long
after you wash

FOR DAILY
USE

NET WT 5 OZ (141 g)